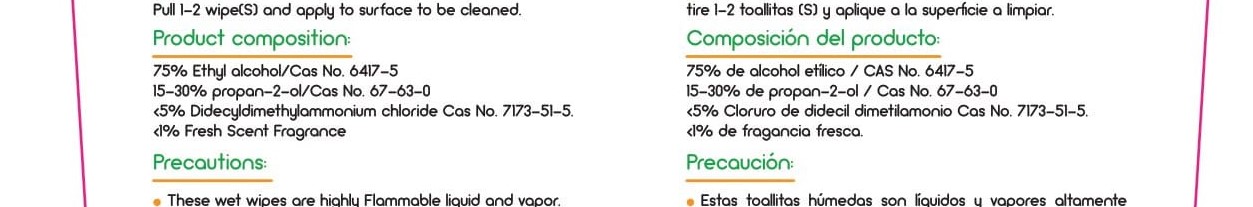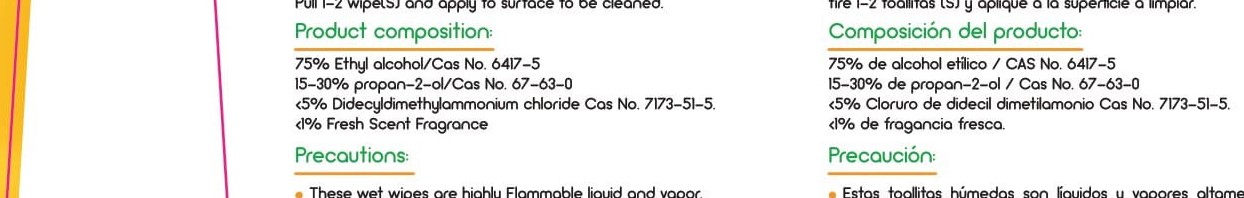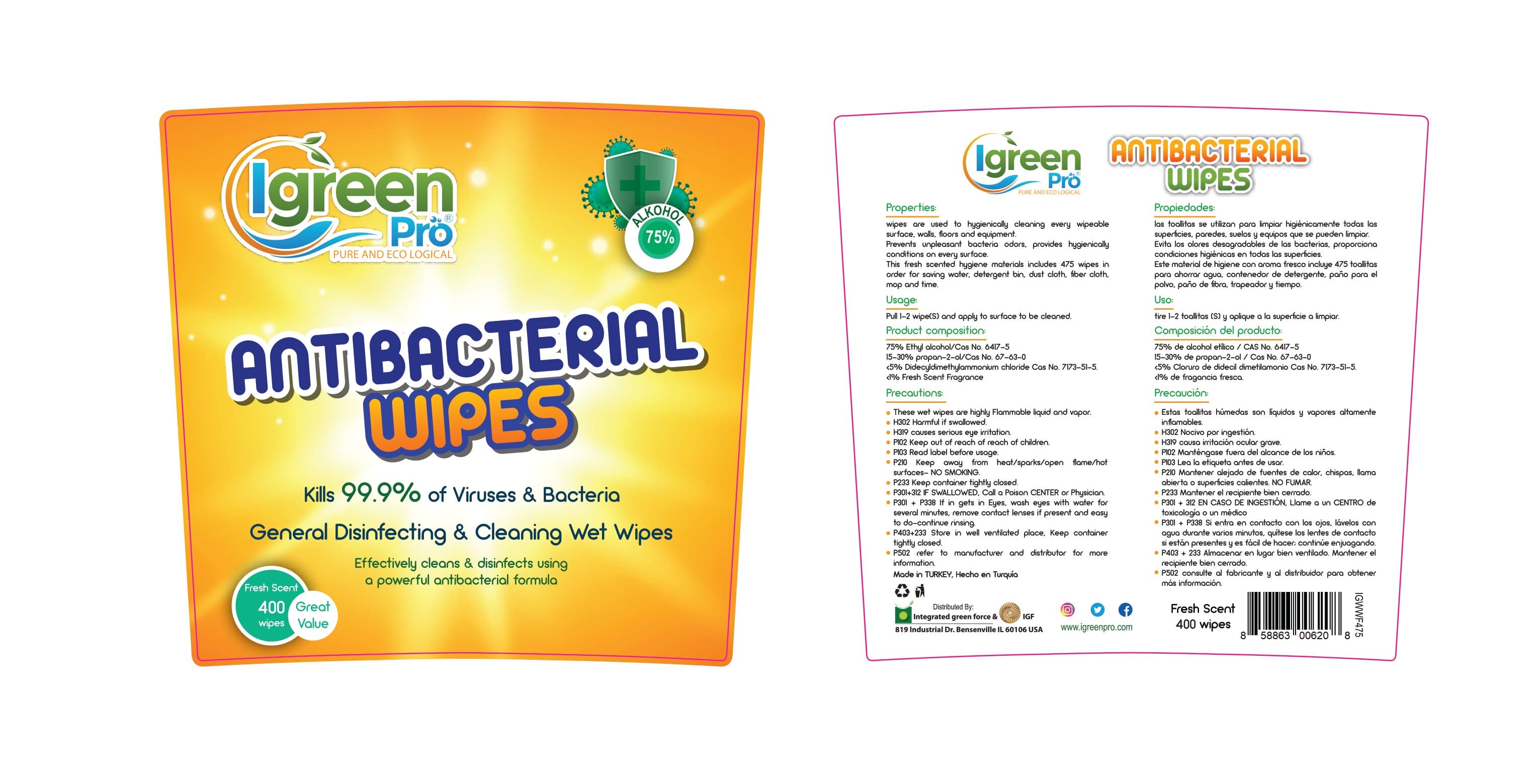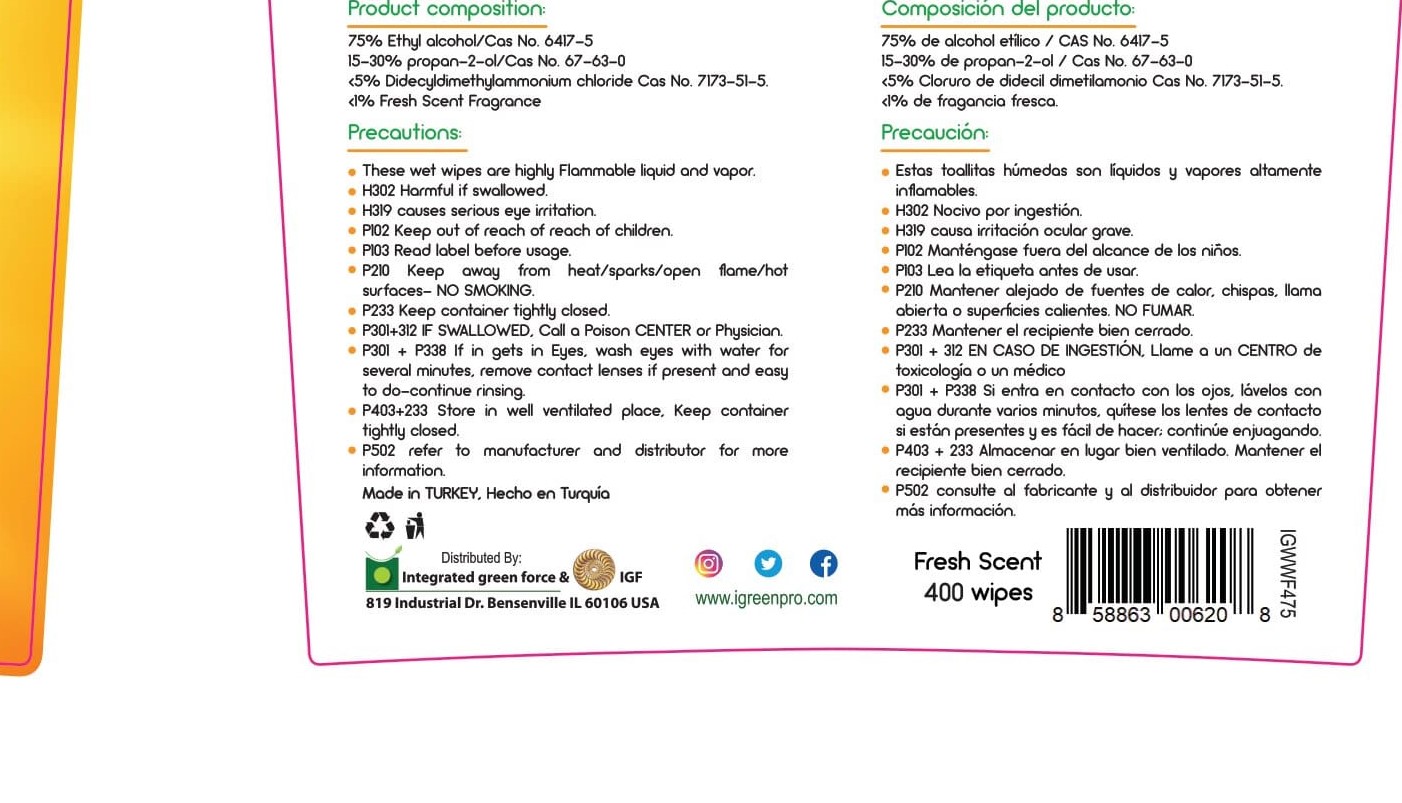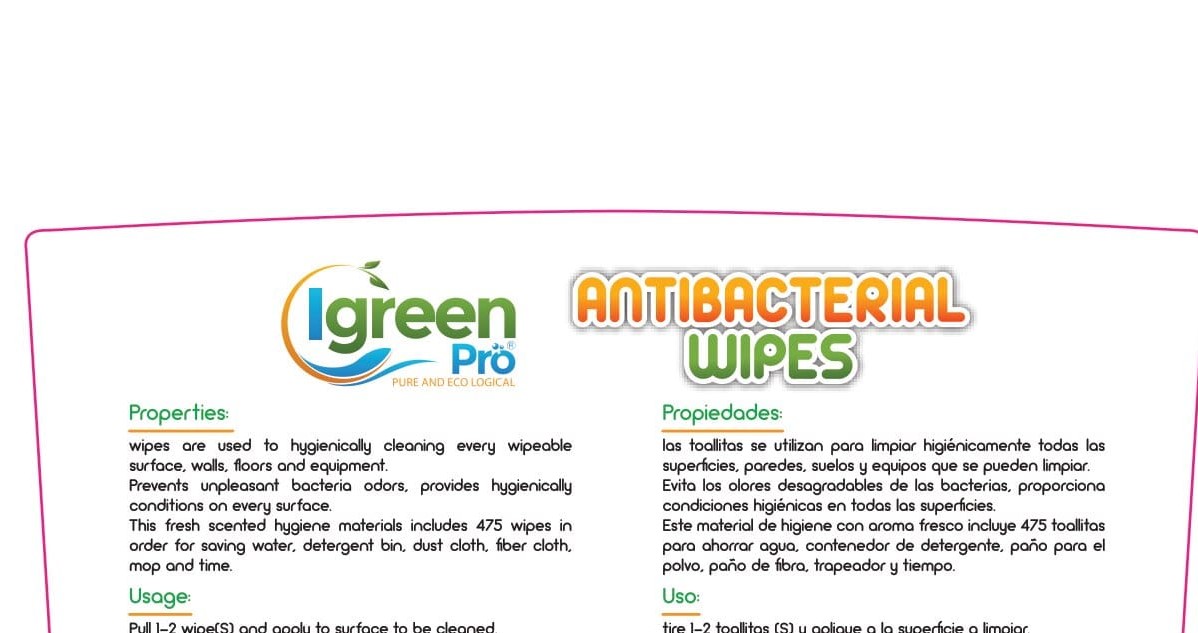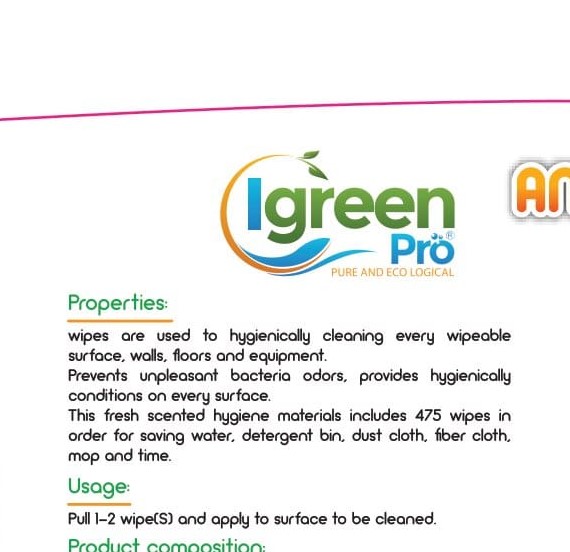 DRUG LABEL: Antibacterial Wipes
NDC: 78311-350 | Form: CLOTH
Manufacturer: Integrated Green Force, LLC
Category: otc | Type: HUMAN OTC DRUG LABEL
Date: 20210304

ACTIVE INGREDIENTS: ISOPROPYL ALCOHOL 1.4798 g/1.4798 g
INACTIVE INGREDIENTS: DIDECYLDIMONIUM CHLORIDE; .BETA.-AMYLOID PROTEIN-(1-6)-PEPTIDYLGLYCYLGLYCYL-L-CYSTEINE-3-(2,5-DIOXO-2,5-DIHYDRO-1H-PYRROLE-1-YL)-N-(6-((2,5-DIOXOPYRROLIDIN-1-YL)OXY)-6-OXOHEXYL)PROPANAMIDE-ALANINE

Antibacterial wipes